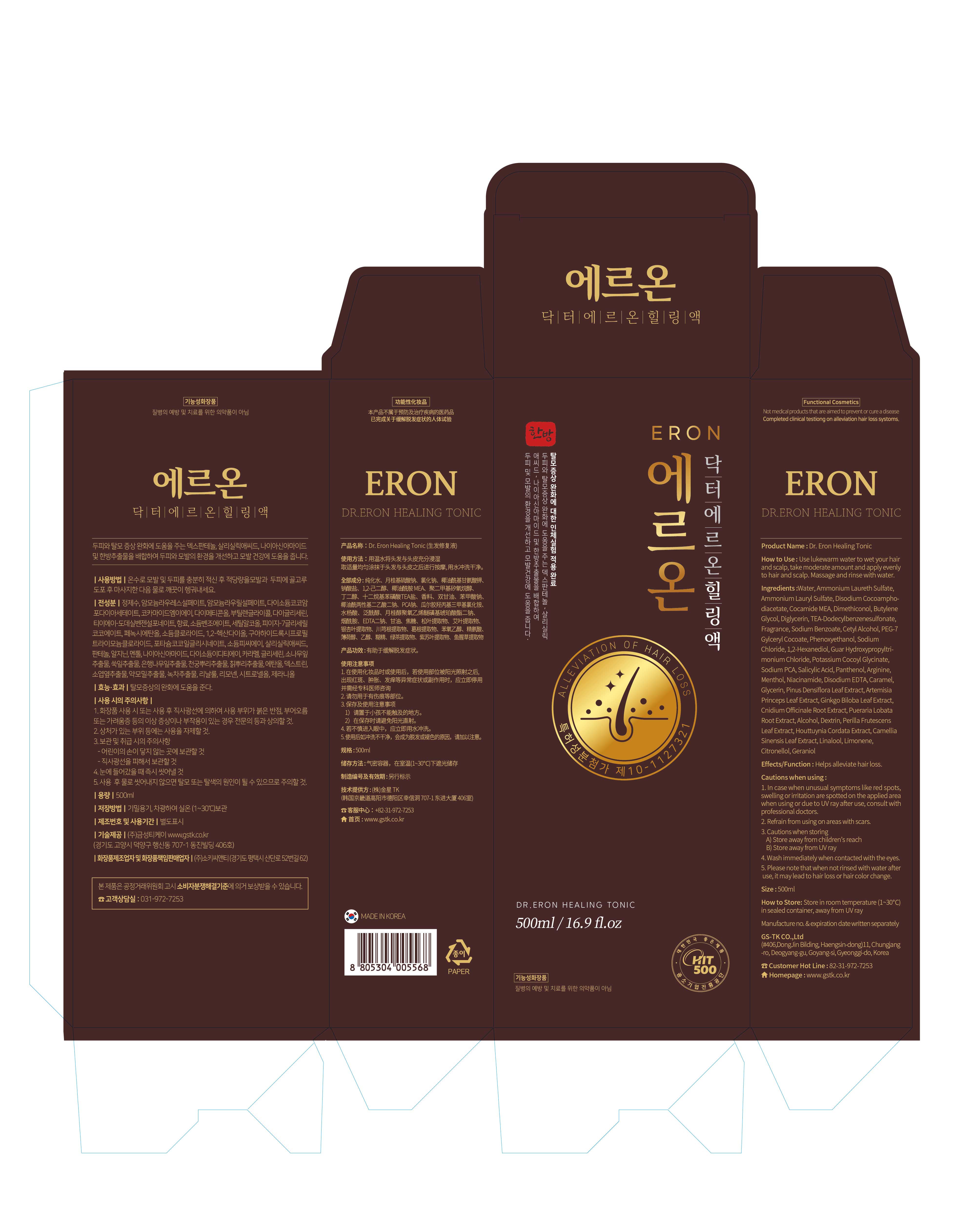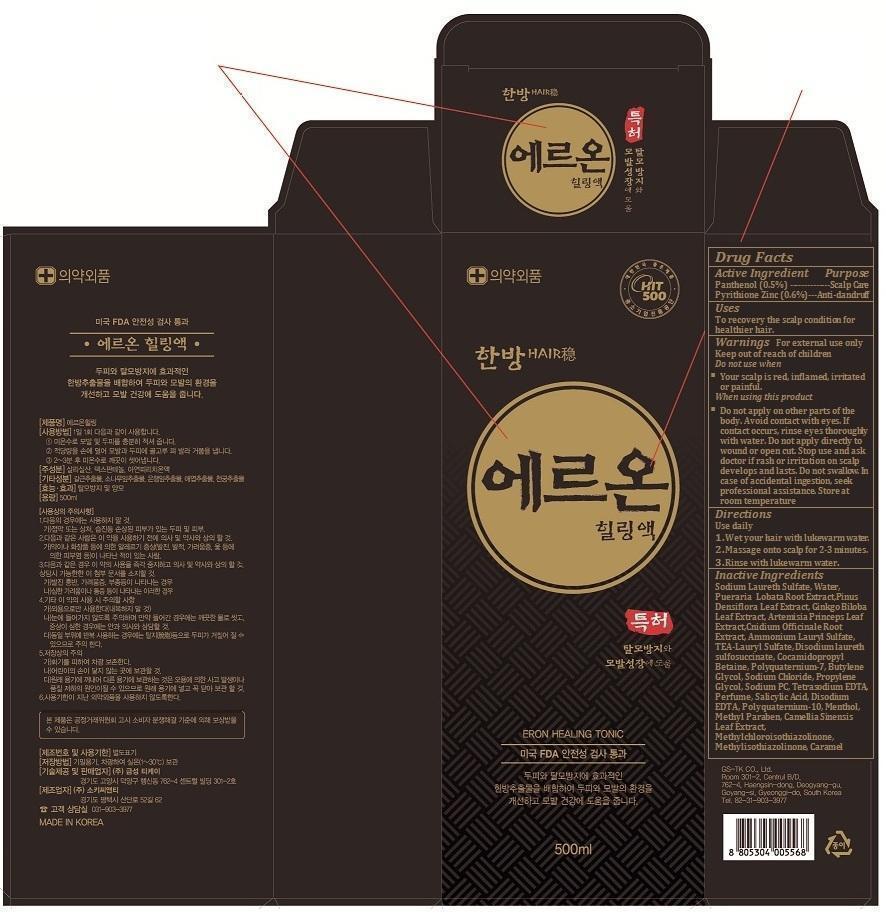 DRUG LABEL: Eron Healing Tonic
NDC: 61558-100 | Form: SHAMPOO
Manufacturer: Geumseong TK
Category: otc | Type: HUMAN OTC DRUG LABEL
Date: 20250605

ACTIVE INGREDIENTS: PYRITHIONE ZINC 3 g/500 mL; PANTHENOL 2.5 g/500 mL
INACTIVE INGREDIENTS: SODIUM LAURETH SULFATE; WATER; AMMONIUM LAURYL SULFATE; DISODIUM LAURETH SULFOSUCCINATE; COCAMIDOPROPYL BETAINE; POLYQUATERNIUM-7 (70/30 ACRYLAMIDE/DADMAC; 1600 KD); BUTYLENE GLYCOL; SODIUM CHLORIDE; PROPYLENE GLYCOL; SODIUM PYRROLIDONE CARBOXYLATE; EDETATE SODIUM; SALICYLIC ACID; EDETATE DISODIUM; MENTHOL; METHYLPARABEN; GREEN TEA LEAF; METHYLCHLOROISOTHIAZOLINONE; METHYLISOTHIAZOLINONE; CARAMEL

Eron Healing Tonic

Inactive Ingredients

Sodium Laureth Sulfate, Water, Pueraria Lobata Root Extract,Pinus Densiflora Leaf Extract, Ginkgo Biloba Leaf Extract, Artemisia Princeps Leaf Extract,Cnidium Officinale Root Extract, Ammonium Lauryl Sulfate, TEA-Lauryl Sulfate, Disodium laureth sulfosuccinate, Cocamidopropyl Betaine, Polyquaternium-7, Butylene Glycol, Sodium Chloride, Propylene Glycol, Sodium PC, Tetrasodium EDTA, Perfume, Salicylic Acid, Disodium EDTA, Polyquaternium-10, Menthol, Methyl Paraben, Camellia Sinensis Leaf Extract, Methylchloroisothiazolinone, Methylisothiazolinone, Caramel

Uses

To recovery the scalp condition for healthier hair.

For external use only

Do not use when

§ Your scalp is red, inflamed, irritated or painful.

When using this product

Do not apply on other parts of the body. Avoid contact with eyes. If contact occurs, rinse eyes thoroughly with water. Do not apply directly to wound or open cut. Stop use and ask doctor if rash or irritation on scalp develops and lasts. Do not swallow. In case of accidental ingestion, seek professional assistance. Store at room temperature.

Keep out of reach of children

Directions

Use daily

1. Wet your hair with lukewarm water.

2. Massage onto scalp for 2-3 minutes.

Rinse with lukewarm water.

DOSAGE AND ADMINISTRATION

Use daily

1. Wet your hair with lukewarm water.

2. Massage onto scalp for 2-3 minutes.

Rinse with lukewarm water.

Eron Healing Tonic

Eron Healing Soultion